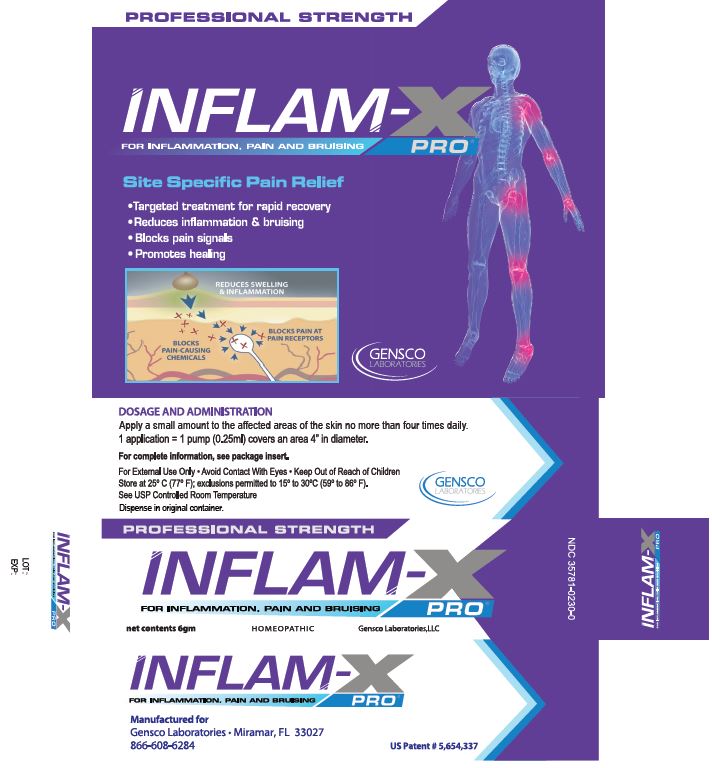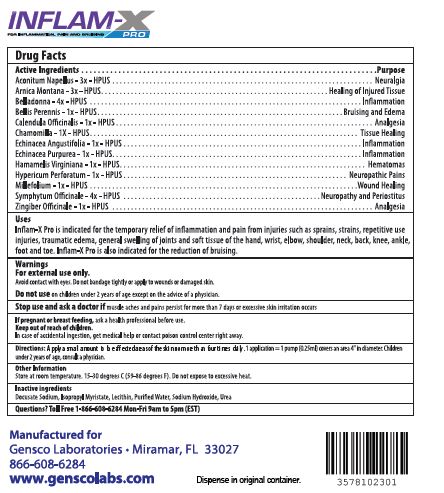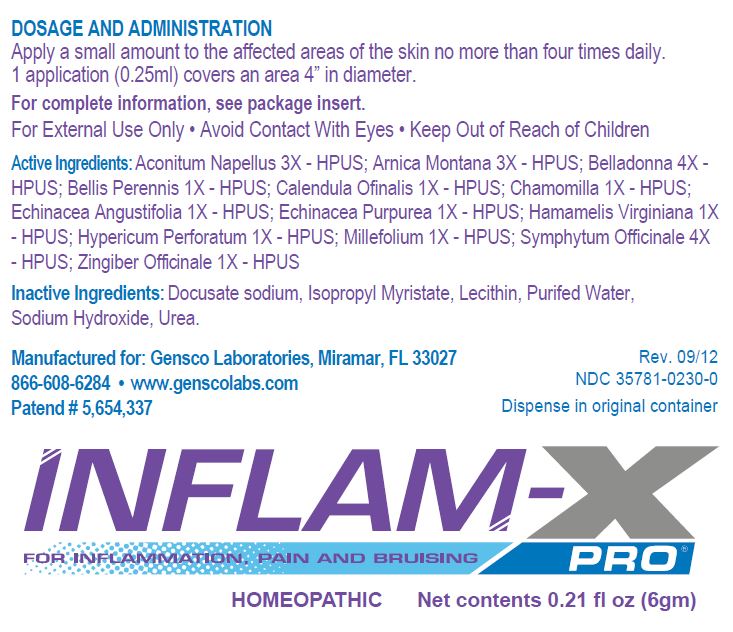 DRUG LABEL: INFLAM-X
NDC: 35781-0230 | Form: GEL
Manufacturer: Gensco Laboratories, LLC
Category: homeopathic | Type: HUMAN OTC DRUG LABEL
Date: 20130501

ACTIVE INGREDIENTS: ACONITUM NAPELLUS 3 [hp_X]/6 mL; ARNICA MONTANA 3 [hp_X]/6 mL; ATROPA BELLADONNA 4 [hp_X]/6 mL; BELLIS PERENNIS 1 [hp_X]/6 mL; CALENDULA OFFICINALIS FLOWER 1 [hp_X]/6 mL; CHAMOMILE 1 [hp_X]/6 mL; ECHINACEA ANGUSTIFOLIA 1 [hp_X]/6 mL; ECHINACEA PURPUREA 1 [hp_X]/6 mL; HAMAMELIS VIRGINIANA ROOT BARK/STEM BARK 1 [hp_X]/6 mL; HYPERICUM PERFORATUM 1 [hp_X]/6 mL; ACHILLEA MILLEFOLIUM 1 [hp_X]/6 mL; COMFREY ROOT 4 [hp_X]/6 mL; GINGER 1 [hp_X]/6 mL
INACTIVE INGREDIENTS: WATER; ISOPROPYL MYRISTATE; UREA; DOCUSATE SODIUM; SODIUM HYDROXIDE

Inflam-X

WARNINGS

FOR EXTERNAL USE ONLY AVOID CONTACT WITH EYES

KEEP OUT OF REACH OF CHILDREN

ACTIVE INGREDIENTS

Aconitum Napellus 3X, Arnica Montana 3X, Belladonna 4X, Bellis Perennis 1X, Calendula Officinalis 1X, Chamomilla 1X, Echinacea Angustifolia 1X, Echinacea Purpurea 1X, Hamamelis Virginiana 1X, Hypericum Perforatum 1X, Millefolium 1X, Symphytum Officinale 3X, Zingiber Officinale 1X.

INACTIVE INGREDIENTS

Purified water, Isopropyl Myristate, lecithin, Urea, Docusate Sodium, Sodium Hydroxide

PACKAGE LABEL

NDC 35781-0230-0 WWW.GENSCOLABS.COM

INDICATIONS AND USAGE

INFLAM-X PRO is a homeopathic topical analgesic gel that contains the ingredients listed below. Homeopathic ingredients have been used since the inception of this science and remain as an effective method of treating select conditions.It is an amber colored odorless gel for use externally to control inflammation and reduce pain.

WARNINGS AND PRECAUTIONS

For external use only. Do not ingest INFLAM-X PRO and avoid contact with the eyes and mucous membranes, wounds, and damaged skin. If condition worsens, or if symptoms persist for more than seven days or clear up and occur again within a few days, you should consult a doctor. If a rash develops, you should discontinue use until rash clears. After the disappearance of rash, you can try INFLAM-X PRO again on a test area and monitor the site for additional results. If no rash or redness results, then you can resume use. However, if the rash persists or redevelops, use should be discontinued.

Keep this product out of reach of children and seek medical help or contact a Poison Control Center immediately if swallowed.

PACKAGE LABEL

US PATENT #5,654,337

NDC 35781-0230-0

WWW.GENSCOLABS.COM

ACTIVE INGREDIENT

DRUG FACTS | PURPOSE
Aconitum Napellus 3X-HPUS | Neuralgia
Arnica Montana 3X-HPUS | Healing of Injured Tissue
Belladonna 4X-HPUS | Inflammation
Bellis Perennis TINC-HPUS | Bruising and Edema
Calendula Officinallis TINC-HPUS | Analgesia
Chamomilla TINC-HPUS | Tissue Healing
Echinacea Angustifolia TINC-HPUS | Inflammation
Echinacea Purpurea TINC-HPUS | Inflammation
Hamamellis Virginiana TINC-HPUS | Hematomas
Hypericum Perforatum TINC-HPUS | Neuropathic Pains
Millefolium TINC-HPUS | Wound healing
Symphytum Officinale 4X-HPUS | Neuropathy and Periostitus
Zingiber Officinale | Inflammation

PURPOSE

INFLAM-X PRO is indicated for the temporary relief of inflammation and pain from injuries such as sprains, strains, repetitive use injuries, traumatic edema, general swelling of joints and soft tissue of the hand, wrist, elbow, shoulder, neck, back, knee, ankle, foot and toe. INFLAM-X PRO is also indicated for the reduction of bruising.

WARNINGS

For external use only. Do not ingest INFLAM-X PRO and avoid contact with the eyes and mucous membranes, wounds, and damaged skin. If condition worsens, or if symptoms persist for more than seven days or clear up and occur again within a few days, you should consult a doctor. If a rash develops, you should discontinue use until rash clears. After the disappearance of rash, you can try INFLAM-X PRO again on a test area and monitor the site for additional results. If no rash or redness results, then you can resume use. However, if the rash persists or redevelops, use should be discontinued.

Keep this product out of reach of children and seek medical help or contact a Poison Control Center immediately if swallowed.

DOSAGE AND ADMINISTRATION

Apply a thin layer (1 drop covers an area of skin 2 inches by 2 inches) to the affected area of the skin 3-4 times daily and rub in gently. Applications of less than 3-4 times a day will not produce optimum results. Excess drops may be wiped from the area. Safe to use on children over age of 2 years.

Other Information

Store at room temperature

Inactive Ingredients

Purified water, Isopropyl Myristate, Lecithin, Urea, Docusate Sodium

QUESTIONS

Questions? Toll Free 1-866-608-6284 Mon-Fri 9AM to 5PM (EST)

PATIENT COUNSELING INFORMATION

Manufactured for

Gensco Laboratories, LLC

Miramar, FL 33027

866.608.6284

US Patent # 5,654,337

www.genscolabs.com